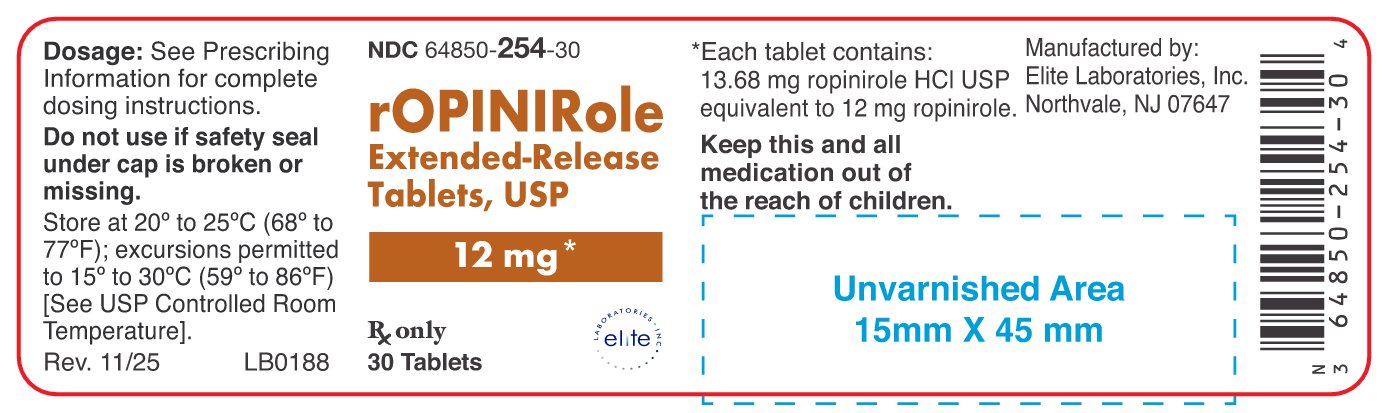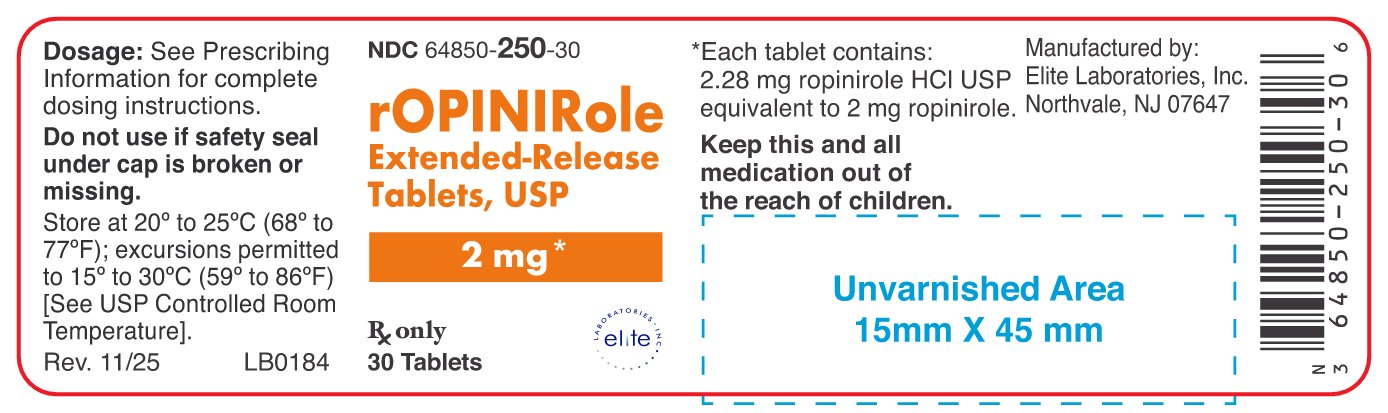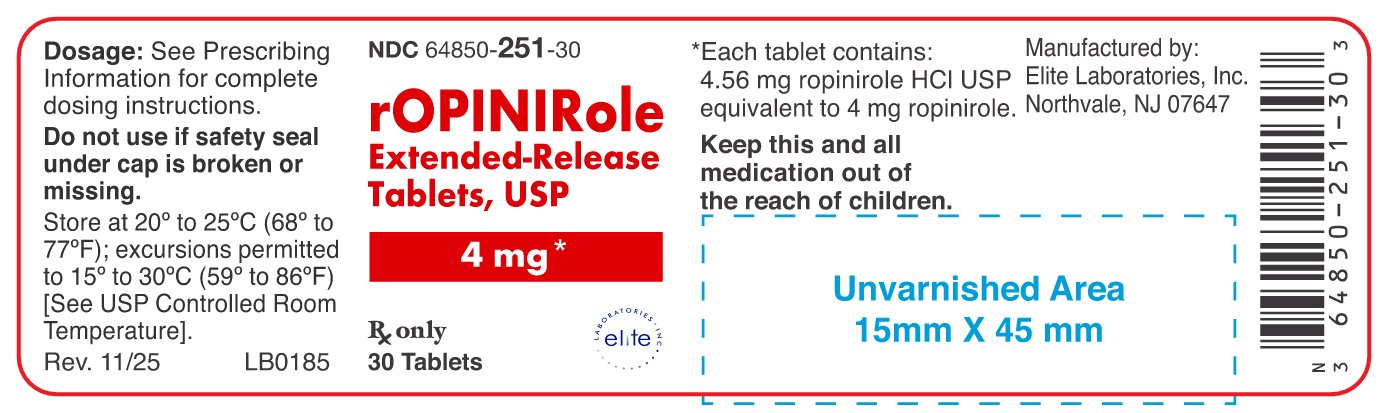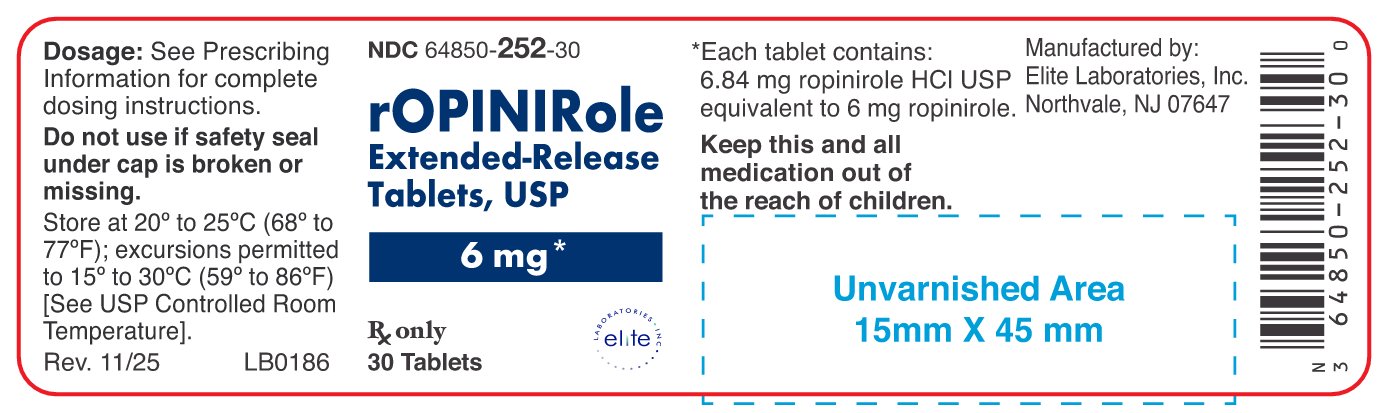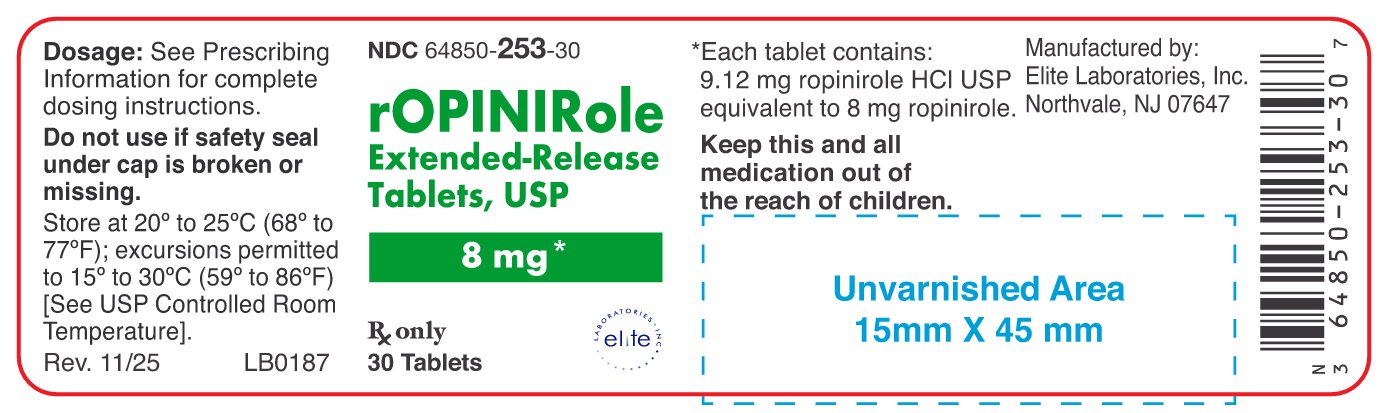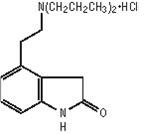 DRUG LABEL: Ropinirole
NDC: 64850-250 | Form: TABLET, EXTENDED RELEASE
Manufacturer: Elite Laboratories,  Inc.
Category: prescription | Type: HUMAN PRESCRIPTION DRUG LABEL
Date: 20251110

ACTIVE INGREDIENTS: Ropinirole Hydrochloride 2 mg/1 1
INACTIVE INGREDIENTS: Lactose Monohydrate; Silicon Dioxide; Hypromellose, Unspecified; magnesium stearate; Croscarmellose Sodium; Maltodextrin; Hydrogenated Castor Oil; Fd&C Blue No. 1; Sodium Carbonate; Sodium Bicarbonate; Dimethicone; Polyethylene Glycol, Unspecified

HIGHLIGHTS OF PRESCRIBING INFORMATION

These highlights do not include all the information needed to use ROPINIROLE EXTENDED-RELEASE TABLETS safely and effectively. See full prescribing information for ROPINIROLE EXTENDED-RELEASE TABLETS.
ROPINIROLE extended-release tablets, for oral use
Initial U.S. Approval: 1997

1 INDICATIONS AND USAGE

Ropinirole extended-release tablets are non-ergoline dopamine agonist indicated for the treatment of Parkinson’s disease. (1)

2 DOSAGE AND ADMINISTRATION

- Ropinirole extended-release tablets are taken once daily, with or without food; tablets must be swallowed whole and not be chewed, crushed, or divided (2.1)
- The recommended starting dose is 2 mg taken once daily for 1 to 2 weeks, the dose should be increased by 2 mg/day at 1 week or longer intervals. The maximum recommended dose of ropinirole extended release tablets is 24 mg/day (2.2, 14.2)
- Renal Impairment: In patients with end-stage renal disease on hemodialysis, the maximum recommended dose is 18 mg/day (2.2)
- If ropinirole extended-release tablets must be discontinued, it should be tapered gradually over a 7-day period, retitration of ropinirole extended-release tablets may be warranted if therapy is interrupted (2.1, 2.2)
- Patients may be switched directly from immediate-release ropinirole to ropinirole extended-release tablets, the initial switching dose of ropinirole extended-release tablets should approximately match the total daily dose of immediate-release ropinirole (2.3)

3 DOSAGE FORMS AND STRENGTHS

Tablets: 2 mg, 4 mg, 6 mg, 8 mg, and 12 mg (3)

4 CONTRAINDICATIONS

History of hypersensitivity/allergic reaction (including urticaria, angioedema, rash, pruritus) to ropinirole or to any of the excipients (4)

5 WARNINGS AND PRECAUTIONS

- Sudden onset of sleep and somnolence may occur (5.1)
- Syncope may occur (5.2)
- Hypotension, including orthostatic hypotension may occur (5.3)
- Elevation of blood pressure and changes in heart rate may occur (5.4)
- May cause hallucinations and psychotic-like behaviors (5.5)
- May cause or exacerbate dyskinesia (5.6)
- May cause problems with impulse control or compulsive behaviors (5.7)

6 ADVERSE REACTIONS

- Most common adverse reactions (incidence for ropinirole extended-release tablets all doses at least 5% greater than placebo in either a flexible- or fixed-dose study) in patients with advanced Parkinson’s disease were nausea, dyskinesia, dizziness, and hallucination (6.1)
- Most common adverse reactions (incidence for ropinirole extended-release tablets all doses at least 5% greater than placebo in fixed-dose study) in patients with early Parkinson’s disease not taking L-dopa were nausea, somnolence, sudden onset of sleep, hypertension, and headache. In a flexible-dose study in patients with early Parkinson's, the most common adverse reactions (at least 5% incidence for ropinirole extended-release tablets) were nausea, somnolence, abdominal pain/discomfort, dizziness, headache, and constipation. (6.1)

To report SUSPECTED ADVERSE REACTIONS, contact Elite Laboratories, Inc. at 1-888-852-6657 or FDA at 1-800-FDA-1088 or www.fda.gov/medwatch.

7 DRUG INTERACTIONS

- Inhibitors or inducers of CYP1A2: May alter the clearance of ropinirole; dose adjustment of ropinirole extended-release tablets may be required (7.1, 12.3)
- Hormone replacement therapy (HRT): Starting or stopping HRT treatment may require dose adjustment of ropinirole extended-release tablets (7.2, 12.3)
- Dopamine antagonists (e.g., neuroleptics, metoclopramide): May reduce efficacy of ropinirole extended-release tablets (7.3)

8 USE IN SPECIFIC POPULATIONS

Pregnancy: Based on animal data, may cause fetal harm. (8.1)

See 17 for PATIENT COUNSELING INFORMATION and FDA-approved patient labeling.

Revised: 11/2025

FULL PRESCRIBING INFORMATION

1 INDICATIONS AND USAGE

Ropinirole extended-release tablets are indicated for the treatment of Parkinson's disease.

2 DOSAGE AND ADMINISTRATION

2.1 General Dosing Recommendations

- Ropinirole extended-release tablets are taken once daily, with or without food [see Clinical Pharmacology (12.3)].
- Tablets must be swallowed whole and must not be chewed, crushed, or divided.
- If a significant interruption in therapy with ropinirole extended-release tablets has occurred, retitration of therapy may be warranted.

2.2 Dosing for Parkinson’s Disease

The recommended starting dose of ropinirole extended-release tablets is 2 mg taken once daily for 1 to 2 weeks, followed by increases of 2 mg/day at weekly or longer intervals, based on therapeutic response and tolerability. Monitor patients at least weekly during dose titration. Too rapid a rate of titration may lead to the selection of a dose that does not provide additional benefit, but increases the risk of adverse reactions.

In fixed-dose studies designed to characterize the dose response to ropinirole extended-release tablets, there was no additional therapeutic benefit shown in patients with advanced stage Parkinson’s disease taking daily doses greater than 8 mg/day, or with early stage Parkinson’s disease taking doses greater than 12 mg/day [see Clinical Studies (14.1 and 14.2)]. Although the maximum recommended dose of ropinirole extended-release tablets is 24 mg, patients with advanced Parkinson’s disease should generally be maintained at daily doses of 8 mg or lower and patients with early Parkinson’s disease should generally be maintained at daily doses 12 mg or lower.

Ropinirole extended-release tablets should be discontinued gradually over a 7-day period [see Warnings and Precautions (5.9)].

Renal Impairment

No dose adjustment is necessary in patients with moderate renal impairment (creatinine clearance of 30 to 50 mL/min). The recommended initial dose of ropinirole extended-release tablets for patients with end-stage renal disease on hemodialysis is 2 mg once daily. Further dose escalations should be based on tolerability and need for efficacy. The recommended maximum total daily dose is 18 mg/day in patients receiving regular dialysis. Supplemental doses after dialysis are not required. The use of ropinirole extended-release tablets in patients with severe renal impairment without regular dialysis has not been studied.

2.3 Switching from Immediate-Release Ropinirole Tablets to Ropinirole Extended-Release Tablets

Patients may be switched directly from immediate-release ropinirole to ropinirole extended-release tablets. The initial dose of ropinirole extended-release tablets should approximately match the total daily dose of the immediate-release formulation of ropinirole, as shown in Table 1.

Table 1. Conversion from Immediate-Release Ropinirole Tablets to Ropinirole Extended-Release Tablets

Immediate-Release Ropinirole Tablets Total Daily Dose (mg) | Ropinirole Extended-Release Tablets Total Daily Dose (mg)
0.75 to 2.25 | 2
3 to 4.5 | 4
6 | 6
7.5 to 9 | 8
12 | 12
15 | 16
18 | 18
21 | 20
24 | 24

Following conversion to ropinirole extended-release tablets, the dose may be adjusted depending on therapeutic response and tolerability [see Dosage and Administration (2.2)].

2.4 Effect of Gastrointestinal Transit Time on Medication Release

Ropinirole extended-release tablets are designed to release medication over a 24-hour period. If rapid gastrointestinal transit occurs, there may be risk of incomplete release of medication and medication residue being passed in the stool.

3 DOSAGE FORMS AND STRENGTHS

- 2 mg: blue biconvex capsule-shaped tablet with ‘ELR2’ on one side and plain on the other.
- 4 mg: beige biconvex capsule-shaped tablet with 'ELR4’ on one side and plain on the other.
- 6 mg: white biconvex capsule-shaped tablet with ‘ELR6’ on one side and plain on the other.
- 8 mg: pink biconvex capsule-shaped tablet with ‘ELR8’ on one side and plain on the other.
- 12 mg: peach biconvex capsule-shaped tablet with ‘ELR12’ on one side and plain on the other.

4 CONTRAINDICATIONS

Ropinirole extended-release tablets are contraindicated in patients known to have a hypersensitivity/allergic reaction (including urticaria, angioedema, rash, pruritus) to ropinirole or any of the excipients.

5 WARNINGS AND PRECAUTIONS

5.1 Falling Asleep during Activities of Daily Living and Somnolence

Patients treated with ropinirole extended-release tablets have reported falling asleep while engaged in activities of daily living, including driving or operating machinery, which sometimes resulted in accidents. Although many of these patients reported somnolence while on ropinirole, some perceived that they had no warning signs such as excessive drowsiness, and believed that they were alert immediately prior to the event. Some have reported these events more than 1 year after initiation of treatment.

Among the 613 patients who received ropinirole extended-release tablets in flexible-dose clinical trials (Study 1 and Study 3), <1% of patients reported sudden onset of sleep and < 1% of patients reported a motor vehicle accident in which it is not known if falling asleep was a contributing factor.

In a placebo-controlled fixed-dose trial in patients with advanced Parkinson’s disease (Study 2), sudden onset of sleep was reported in 4% of 276 patients on ropinirole extended-release tablets compared with 3% of 74 patients on placebo. In a placebo-controlled fixed-dose trial in patients with early Parkinson’s disease (Study 4), sudden onset of sleep was reported in 5% of 146 patients on ropinirole extended-release tablets compared with 0% of 40 patients on placebo [see Adverse Reactions (6.1)]. The incidence of sudden onset of sleep was not dose-related in either trial.

During a placebo-controlled flexible-dose trial in patients with advanced Parkinson’s disease (Study 1), somnolence was reported in 7% of 202 patients on ropinirole extended-release tablets compared with 4% of 191 patients on placebo. During a flexible-dose, active-control, crossover trial in early Parkinson’s disease (Study 3), somnolence was reported in 11% of 140 patients on ropinirole extended-release tablets compared with 15% of 149 patients on an immediate-release formulation of REQUIP [see Adverse Reactions (6.1)].

In a placebo-controlled fixed-dose trial in patients with advanced Parkinson’s disease (Study 2), somnolence was reported in 8% of 276 patients on ropinirole extended-release tablets compared with 5% of 74 patients on placebo. In a placebo-controlled fixed-dose trial in patients with early Parkinson’s disease (Study 4), somnolence was reported in 10% of 146 patients on ropinirole extended-release tablets compared with 5% of 40 patients on placebo [see Adverse Reactions (6.1)]. The frequency of reported somnolence was not dose-related.

It has been reported that falling asleep while engaged in activities of daily living usually occurs in a setting of pre-existing somnolence, although patients may not give such a history. For this reason, prescribers should reassess patients for drowsiness or sleepiness, especially since some of the events occur well after the start of treatment. Prescribers should also be aware that patients may not acknowledge drowsiness or sleepiness until directly questioned about drowsiness or sleepiness during specific activities.

Before initiating treatment with ropinirole extended-release tablets, patients should be advised of the potential to develop drowsiness and specifically asked about factors that may increase the risk with ropinirole extended-release tablets such as concomitant sedating medications or alcohol, the presence of sleep disorders, and concomitant medications that increase ropinirole plasma levels (e.g., ciprofloxacin) [see Drug Interactions (7.1)]. If a patient develops significant daytime sleepiness or episodes of falling asleep during activities that require active participation (e.g., driving a motor vehicle, conversations, eating), ropinirole extended-release tablets should ordinarily be discontinued [see Dosage and Administration (2.2)]. If a decision is made to continue ropinirole extended-release tablets, patients should be advised to not drive and to avoid other potentially dangerous activities. There is insufficient information to establish that dose reduction will eliminate episodes of falling asleep while engaged in activities of daily living.

5.2 Syncope

Syncope, sometimes associated with bradycardia, was observed in association with treatment with ropinirole extended-release tablets in patients with Parkinson’s disease.

In a placebo-controlled flexible-dose trial in patients with advanced Parkinson's disease (Study 1), syncope occurred in 1% of patients on ropinirole extended-release tablets compared with 0% of patients on placebo [see Adverse Reactions (6.1)].

In the placebo-controlled fixed-dose trials (Study 2 and Study 4), one patient on ropinirole extended-release tablets with advanced Parkinson's disease) and one patient on ropinirole extended-release tablets with early Parkinson's disease experienced syncope during the titration period for ropinirole extended-release tablets. Both patients discontinued prematurely from the respective trials.

Because the trials conducted with ropinirole extended-release tablets excluded patients with significant cardiovascular disease, patients with significant cardiovascular disease should be treated with caution.

5.3 Hypotension/Orthostatic Hypotension

Patients with Parkinson's disease may have impaired ability to respond normally to a fall in blood pressure after standing from lying down or seated position. Patients on ropinirole extended-release tablets should be monitored for signs and symptoms of orthostatic hypotension, especially during dose escalation, and should be informed of the risk for syncope and hypotension [see Patient Counseling Information (17)].

In a placebo-controlled flexible-dose trial in patients with advanced Parkinson’s disease (Study 1), hypotension was reported as an adverse reaction in 2% of patients on ropinirole extended-release tablets, compared with 0% of patients on placebo. In this study, orthostatic hypotension was reported as an adverse reaction in 5% of patients on ropinirole extended-release tablets, and 1% of patients on placebo [see Adverse Reactions (6.1)]. Some patients experienced hypotension or orthostatic hypotension that started in the titration and persisted into the maintenance period. There was also a higher incidence for the combined adverse reaction terms of “hypotension”, “orthostatic hypotension”, “dizziness”, “vertigo”, and "blood pressure decreased” in 7% of patients on ropinirole extended-release tablets compared with 3% of patients on placebo. The increased incidence of those events with ropinirole extended-release tablets was observed in a setting in which patients were very carefully titrated, and patients with clinically relevant cardiovascular disease or symptomatic orthostatic hypotension at baseline had been excluded from this trial. The frequency of orthostatic hypotension (systolic blood pressure decrements ≥20 mm Hg) at any time during the trial was 38% for ropinirole extended-release tablets vs. 31% for placebo.

In a placebo-controlled fixed-dose trial in patients with advanced Parkinson’s disease (Study 2), a decrease in standing systolic blood pressure of ≥20 mm Hg was observed in 26% of patients on ropinirole extended-release tablets compared with 18% of patients on placebo.

In a placebo-controlled fixed-dose trial of patients with early Parkinson's disease (Study 4), a decrease in standing systolic blood pressure of ≥20 mm Hg was observed in 14% of patients on ropinirole extended-release tablets compared with 10% of patients on placebo.

Significant decrements in blood pressure unrelated to standing were also reported in some patients taking ropinirole extended-release tablets.

5.4 Elevation of Blood Pressure and Changes in Heart Rate

The potential for elevation in blood pressure and changes in heart rate should be considered when treating patients with cardiovascular disease with ropinirole extended-release tablets.

In a placebo-controlled flexible-dose trial in patients with advanced Parkinson’s disease (Study 1), the frequency of systolic blood pressure increase (≥40mm Hg) in the semi-supine position was 8% of patients on ropinirole extended-release tablets vs. 5% of patients on placebo. In the standing position, the frequency of systolic blood pressure increase (≥40 mm Hg) was 9% for ropinirole extended-release tablets vs. 6% for placebo. There was no clear effect of ropinirole extended-release tablets on average heart rate.

In a placebo-controlled fixed-dose trial in patients with advanced Parkinson’s disease (Study 2), hypertension was reported as an adverse reaction in 3% of patients on ropinirole extended-release tablets, compared with 1% of patients on placebo [see Adverse Reactions (6.1)].

In a placebo-controlled, fixed-dose trial in patients with early Parkinson’s disease (Study 4), hypertension was reported as an adverse reaction in 5% of patients on ropinirole extended-release tablets, compared with 0% of patients on placebo [see Adverse Reactions (6.1)].

5.5 Hallucinations/Psychotic-Like Behavior

In a placebo-controlled flexible-dose trial in patients with advanced Parkinson’s disease (Study 1), 8% of patients on ropinirole extended-release tablets reported hallucination, compared with 2% of patients on placebo [see Adverse Reactions (6.1)]. Hallucinations led to discontinuation of treatment in 2% of patients on ropinirole extended-release tablets and 1% of patients on placebo. The incidence of hallucination was increased in elderly patients (i.e., older than 65 years) treated with ropinirole extended-release tablets [see Use in Specific Populations (8.5)].

In a placebo-controlled fixed-dose trial in patients with advanced Parkinson’s disease (Study 2), the incidence of hallucination was 3% in patients on ropinirole extended-release tablets compared with 0% in patients on placebo [see Adverse Reactions (6.1)]. The most common adverse reaction associated with study discontinuation for any dose of ropinirole extended-release tablets was hallucination (2%).

Postmarketing reports indicate that patients with Parkinson’s disease may experience new or worsening mental status and behavioral changes, which may be severe, including psychotic-like behavior during treatment with ropinirole extended-release tablets or after starting or increasing the dose of ropinirole extended-release tablets. Other drugs prescribed to improve the symptoms of Parkinson’s disease can have similar effects on thinking and behavior. This abnormal thinking and behavior can consist of one or more of a variety of manifestations including paranoid ideation, delusions, hallucinations, confusion, psychotic-like behavior, symptoms of mania (e.g., insomnia, psychomotor agitation), disorientation, aggressive behavior, agitation, and delirium.

Patients with a major psychotic disorder should ordinarily not be treated with ropinirole extended-release tablets because of the risk of exacerbating the psychosis. In addition, certain medications used to treat psychosis may exacerbate the symptoms of Parkinson’s disease and may decrease the effectiveness of ropinirole extended-release tablets [see Drug Interactions (7.3)].

5.6 Dyskinesia

Ropinirole extended-release tablets may cause or exacerbate pre-existing dyskinesia in patients treated with L-dopa for Parkinson’s disease.

In a placebo-controlled flexible-dose trial in patients with advanced Parkinson’s disease (Study 1), the incidence of dyskinesia was 13% in patients on ropinirole extended-release tablets and 3% in patients on placebo [see Adverse Reactions (6.1)].

In a placebo-controlled, fixed-dose trial in patients with advanced Parkinson’s disease (Study 2), the incidence of dyskinesia was 7% in patients on ropinirole extended-release tablets compared with 1% in patients on placebo [see Adverse Reactions (6.1)].

Decreasing the dose of dopaminergic medications may ameliorate this adverse reaction.

5.7 Impulse Control/Compulsive Behaviors

Reports suggest that patients can experience intense urges to gamble, increased sexual urges, intense urges to spend money, binge or compulsive eating, and/or other intense urges, and the inability to control these urges while taking one or more of the medications, including ropinirole extended-release tablets, that increase central dopaminergic tone. In some cases, although not all, these urges were reported to have stopped when the dose was reduced or the medication was discontinued. Because patients may not recognize these behaviors as abnormal, it is important for prescribers to specifically ask patients or their caregivers about the development of new or increased gambling urges, sexual urges, uncontrolled spending, binge or compulsive eating, or other urges while being treated with ropinirole extended-release tablets for Parkinson's disease. Physicians should consider dose reduction or stopping the medication if a patient develops such urges while taking ropinirole extended-release tablets.

5.8 Withdrawal-Emergent Hyperpyrexia and Confusion

A symptom complex resembling the neuroleptic malignant syndrome (characterized by elevated temperature, muscular rigidity, altered consciousness, and autonomic instability), with no other obvious etiology, has been reported in association with rapid dose reduction of, withdrawal of, or changes in, dopaminergic therapy. Therefore, it is recommended that the dose be tapered at the end of treatment with ropinirole extended-release tablets as a prophylactic measure [see Dosage and Administration (2.2)].

5.9 Withdrawal Symptoms

Symptoms including insomnia, apathy, anxiety, depression, fatigue, sweating, and pain have been reported during taper or after discontinuation of dopamine agonists, including ropinirole extended-release tablets. These symptoms generally do not respond to levodopa.

Prior to discontinuation of ropinirole extended-release tablets, patients should be informed about the potential withdrawal symptoms and monitored during and after discontinuation. In case of severe withdrawal symptoms, a trial re-administration of a dopamine agonist at the lowest effective dose may be considered.

5.10 Fibrotic Complications

Cases of retroperitoneal fibrosis, pulmonary infiltrates, pleural effusion, pleural thickening, pericarditis, and cardiac valvulopathy have been reported in some patients treated with ergot-derived dopaminergic agents. While these complications may resolve when the drug is discontinued, complete resolution does not always occur.

Although these adverse reactions are believed to be related to the ergoline structure of these compounds, whether other, non-ergot-derived dopamine agonists such as ropinirole, can cause them is unknown.

Cases of possible fibrotic complications, including pleural effusion, pleural fibrosis, interstitial lung disease, and cardiac valvulopathy have been reported in the development program and postmarketing experience for ropinirole. In the clinical development program (N=613), 2 patients treated with ropinirole extended-release tablets had pleural effusion. While the evidence is not sufficient to establish a causal relationship between ropinirole and these fibrotic complications, a contribution of ropinirole cannot be excluded.

5.11 Retinal Pathology

Retinal degeneration was observed in albino rats in the 2-year carcinogenicity study at all dose stested. The lowest dose tested (1.5 mg/kg/day) is less than the maximum recommended human dose (MRHD) of 24 mg/day on a mg/m^2 basis. Retinal degeneration was not observed in a 3-month study in pigmented rats, in a 2-year carcinogenicity study in albino mice, or in 1-yearstudies in monkeys or albino rats. The significance of this effect for humans has not been established, but involves disruption of a mechanism that is universally present in vertebrates(e.g., disk shedding).

Ocular electroretinogram assessments were conducted during a 2-year, double-blind, multicenter, flexible-dose, L-dopa-controlled clinical trial of immediate-release ropinirole in patients with Parkinson’s disease; 156 patients (78 on immediate-release ropinirole, mean dose: 11.9 mg/day and 78 on L-dopa, mean dose: 555.2 mg/day) were evaluated for evidence of retinal dysfunction through electroretinograms. There was no clinically meaningful difference between the treatment groups in retinal function over the duration of the trial.

5.12 Binding to Melanin

Ropinirole binds to melanin-containing tissues (e.g., eyes, skin) in pigmented rats. After a single dose, long-term retention of drug was demonstrated, with a half-life in the eye of 20 days.

6 ADVERSE REACTIONS

The following adverse reactions are described in more detail in other sections of the label:

- Hypersensitivity [see Contraindications (4)]
- Falling asleep during activities of daily living and somnolence [see Warnings and Precautions (5.1)]
- Syncope [see Warnings and Precautions (5.2)]
- Hypotension/orthostatic hypotension [see Warnings and Precautions (5.3)]
- Elevation of blood pressure and changes in heart rate [see Warnings and Precautions (5.4)]
- Hallucinations/psychotic-like behavior [see Warnings and Precautions (5.5)]
- Dyskinesia [see Warnings and Precautions (5.6)]
- Impulse control/compulsive behaviors [see Warnings and Precautions (5.7)]
- Withdrawal-emergent hyperpyrexia and confusion [see Warnings and Precautions (5.8)]
- Withdrawal symptoms [see Warnings and Precautions (5.9)]
- Fibrotic complications [see Warnings and Precautions (5.10)]
- Retinal pathology [see Warnings and Precautions (5.11)]

6.1 Clinical Trials Experience

Because clinical trials are conducted under widely varying conditions, adverse reaction rates observed in the clinical trials of a drug cannot be directly compared with rates in the clinical trials of another drug (or of another development program of a different formulation of the same drug) and may not reflect the rates observed in practice.

During the premarketing development of ropinirole extended-release tablets, patients with advanced Parkinson’s disease received ropinirole extended-release tablets or placebo as adjunctive therapy with L-dopa in a flexible-dose clinical trial. In a flexible-dose trial, patients with early Parkinson's disease were treated with ropinirole extended-release tablets or the immediate-release formulation of REQUIP without L-dopa. In addition, placebo-controlled, fixed-dose, postmarketing trials evaluated the dose response of ropinirole extended-release tablets in patients with advanced Parkinson’s disease taking L-dopa and in patients with early Parkinson's disease without concomitant L-dopa.

Advanced Parkinson’s Disease (with L-dopa)

Study 1 was a 24-week, double-blind, placebo-controlled, flexible-dose trial in patients with advanced Parkinson's disease. In Study 1, the most commonly observed adverse reactions inpatients treated with ropinirole extended-release tablets (incidence at least 5% greater thanplacebo) were dyskinesia, nausea, dizziness, and hallucinations.

In Study 1, approximately 6% of patients treated with ropinirole extended-release tablets discontinued treatment due to adverse reactions compared with 5% of patients who received placebo. The most common adverse reaction in patients treated with ropinirole extended-release tablets causing discontinuation of treatment with ropinirole extended-release tablets in Study 1 was hallucination (2%).

Table 2 lists adverse reactions that occurred in at least 2% (and were numerically greater than placebo) of patients with advanced Parkinson’s disease treated with ropinirole extended-release tablets who participated in Study 1. In this trial, either ropinirole extended-release tablets or placebo was used as an adjunct to L-dopa.

Table 2. Incidence of Adverse Reactions in a Placebo-Controlled Flexible-Dose Trial in Advanced Stage Parkinson's Disease in Patients Taking L-dopa (Study 1) (Events ≥2% of Patients Treated with Ropinirole Extended-Release Tablets and More Common than on Placebo)a

Body System/Adverse Reaction | Ropinirole Extended-Release Tablets (n = 202) % | Placebo (n = 191) %
Ear and labyrinth disorders
Vertigo | 4 | 2
Gastrointestinal disorders
Nausea | 11 | 4
Abdominal pain/discomfort | 6 | 3
Constipation | 4 | 2
Diarrhea | 3 | 2
Dry mouth | 2 | <1
General disorders
Edema peripheral | 4 | 1
Injury, poisoning, and procedural complications
Fallb | 2 | 1
Musculoskeletal and connective tissue disorders
Back pain | 3 | 2
Nervous system disorders
Dyskinesiab | 13 | 3
Dizziness | 8 | 3
Somnolence | 7 | 4
Psychiatric disorders
Hallucination | 8 | 2
Anxiety | 2 | 1
Vascular disorders
Orthostatic hypotension | 5 | 1
Hypertensionb | 3 | 2
Hypotension | 2 | 0

a Patients may have reported multiple adverse reactions during the trial or at discontinuation;thus, patients may be included in more than one category.

b Dose-related.

Although this trial was not designed for optimally characterizing dose-related adverse reactions, there was a suggestion (based upon comparison of incidence of adverse reactions across dose ranges for ropinirole extended-release tablets and placebo) that the incidence for dyskinesia, hypertension, and fall was dose-related to ropinirole extended-release tablets.

During the titration phase, the incidence of adverse reactions in descending order of percent treatment difference was dyskinesia, nausea, abdominal pain/discomfort, orthostatic hypotension, dizziness, vertigo, hypertension, peripheral edema, and dry mouth. During the maintenance phase, the most frequently observed adverse reactions were dyskinesia, nausea, dizziness, hallucination, somnolence, fall, hypertension, abnormal dreams, constipation, chest pain, bronchitis, and nasopharyngitis. Some adverse reactions developing in the titration phase persisted (≥7 days) into the maintenance phase. These “persistent” adverse reactions included dyskinesia, hallucination, orthostatic hypotension, and dry mouth.

The incidence of adverse reactions was similar in women and men.

Study 2 was an 18-week, double-blind, placebo-controlled, fixed-dose, dose-response trial in patients with advanced Parkinson’s disease. In Study 2, approximately 7% of patients treated with any dose of ropinirole extended-release tablets discontinued prematurely during the titration phase because of adverse reactions, compared with 4% of patients on placebo. The percentage of patients who discontinued from the study because of an adverse reaction was 4% for ropinirole extended-release tablets 4 mg, 9% for ropinirole extended-release tablets 8 mg, 8% for ropinirole extended-release tablets 12 mg, 8% for ropinirole extended-release tablets 16 mg, and 0% for ropinirole extended-release tablets 24 mg [see Warnings and Precautions (5.2, 5.5)].Table 3 lists adverse reactions with an incidence of at least 5% of patients in any dose group of ropinirole extended-release tablets and numerically higher than on placebo in Study 2. The most common adverse reaction (incidence for ropinirole extended-release tablets all doses at least 5% greater than placebo) was dyskinesia.

Table 3. Incidence of Adverse Reactions in a Placebo-Controlled Fixed-Dose Trial in Advanced Stage Parkinson’s Disease in Patients Taking L-dopa (Study 2) (Events ≥5% of Patients Treated with any Dose of Ropinirole Extended-Release Tablets and More Common than on Placebo)

Adverse Reaction | Ropinirole Extended-Release Tablets
Adverse Reaction | Placebo N = 74 % | 4 mg N = 25 % | 8 mg N = 76 % | 12 mg N = 75 % | 16 mg N = 75 % | 24 mg N = 25 % | All Doses N = 276 %
Nervous system disorders
Somnolence | 5 | 4 | 5 | 12 | 11 | 0 | 8
Dyskinesia | 1 | 4 | 4 | 7 | 11 | 4 | 7
Dizziness | 3 | 8 | 4 | 8 | 5 | 4 | 6
Sudden onset of sleep | 3 | 8 | 5 | 4 | 1 | 0 | 4
Vascular disorders Hypertension | 1 | 8 | 1 | 1 | 4 | 8 | 3
Infections and infestations Nasopharyngitis | 1 | 0 | 3 | 3 | 0 | 8 | 2
Musculoskeletal and connective tissue disorders Arthralgia | 0 | 0 | 3 | 0 | 3 | 8 | 2
Psychiatric disorders Insomnia | 0 | 0 | 0 | 1 | 5 | 0 | 2

Early Parkinson’s Disease (without L-dopa)

Study 3 was a 36-week, flexible-dose crossover trial in patients with early Parkinson’s disease who were first treated with ropinirole extended-release tablets or the immediate-release formulation of REQUIP and then crossed over to treatment with the other formulation. In Study 3, the most commonly observed adverse reactions (≥5%) in patients treated with ropinirole extended-release tablets were nausea (19%), somnolence (11%), abdominal pain/discomfort (7%), dizziness (6%), headache (6%), and constipation (5%).

Study 4 was an 18-week, double-blind, placebo-controlled, fixed-dose, dose-response trial in patients with early Parkinson’s disease. Overall, 7% of patients treated with any dose of ropinirole extended-release tablets, including 6% during the titration phase, discontinued prematurely from the study because of adverse reactions compared with 5% of patients on placebo. The percentage of patients discontinuing prematurely because of an adverse reaction was 8% for ropinirole extended-release tablets 2 mg, 5% for ropinirole extended-release tablets 4 mg, 8% for ropinirole extended-release tablets 8 mg, 5% for ropinirole extended-release tablets 12 mg, and 15% for ropinirole extended-release tablets 24 mg.

Table 4 lists adverse reactions with an incidence of at least 10% of patients in any dose group of ropinirole extended-release tablets and numerically higher than on placebo in Study 4. The most common adverse reactions (incidence for ropinirole extended-release tablets all doses at least 5% greater than placebo) were nausea, somnolence, sudden onset of sleep, hypertension, and headache.

Table 4. Incidence of Adverse Reactions in a Double-Blind, Placebo-Controlled, Fixed- Dose, Trial in Early Stage Parkinson’s Disease (Study 4) (Events ≥10% of Patients Treated with any Dose of Ropinirole Extended-Release Tablets and Greater Percent than on Placebo)

Adverse Reactions | Ropinirole Extended-Release Tablets
Adverse Reactions | Placebo N = 40 % | 2 mg N = 13 % | 4 mg N = 41 % | 8 mg N = 40% | 12 mg N = 39 % | 24 mg N = 13 % | All Doses N = 146 %
Gastrointestinal disorders
Nausea | 8 | 8 | 15 | 33 | 10 | 15 | 18
Vomiting | 5 | 0 | 5 | 10 | 0 | 0 | 4
Nervous system disorders
Somnolence | 5 | 15 | 12 | 10 | 8 | 8 | 10
Headache | 3 | 8 | 10 | 8 | 5 | 15 | 8
Dizziness | 5 | 0 | 5 | 10 | 8 | 8 | 7
Sudden onset of sleep | 0 | 0 | 5 | 0 | 10 | 8 | 5
Vascular disorders
Hypertension | 0 | 0 | 5 | 5 | 3 | 15 | 5
Musculoskeletal and connective tissue disorders
Back pain | 3 | 0 | 5 | 3 | 3 | 15 | 4

Laboratory Abnormalities

In the fixed-dose trial in advanced Parkinson's disease (Study 2), 11% of patients on ropinirole extended-release tablets exhibited a shift in serum creatine phosphokinase (CPK) from normal at baseline to above the normal reference range during treatment, compared with 6% of patients on placebo. There was no clear dose response for abnormal shifts in CPK levels in patients with early or advanced stage Parkinson’s disease in either fixed-dose trial.

In the fixed-dose trial in early Parkinson's disease patients (Study 4), serum CPK shifted during treatment from normal to above the normal reference range in 10% of patients on ropinirole extended-release tablets and in 5% of patients on placebo.

6.2 Adverse Reactions Observed during the Clinical Development of the Immediate-Release Formulation of REQUIP for Parkinson’s Disease (Advanced and Early)

Because clinical trials are conducted under widely varying conditions, adverse reaction rates observed in the clinical trials of a drug cannot be directly compared with rates in the clinical trials of another drug (or of another development program of a different formulation of the same drug) and may not reflect the rates observed in practice.

In patients with advanced Parkinson's disease who were treated with the immediate-release formulation of REQUIP, the most common adverse reactions (≥5% treatment difference from placebo presented in order of decreasing treatment difference frequency) were dyskinesia (21%), somnolence (12%), nausea (12%), dizziness (10%), confusion (7%), hallucinations (6%), headache (5%), and increased sweating (5%). In patients with early Parkinson's disease who were treated with the immediate-release formulation of REQUIP, the most common adverse reactions (≥5% treatment difference from placebo presented in order of decreasing treatment difference frequency) were nausea (38%), somnolence (34%), dizziness (18%), syncope (11%), asthenic condition (11%), viral infection (8%), leg edema (6%), vomiting (5%), and dyspepsia (5%).

6.3 Postmarketing Experience

The following adverse reactions have been identified during postapproval use of ropinirole extended-release tablets.

Because these reactions are reported voluntarily from a population of uncertain size, it is not always possible to reliably estimate their frequency or establish a causal relationship to drug exposure.

General Disorders and Administration Site Conditions

Withdrawal Symptoms [see Warnings and Precautions (5.9)]

7 DRUG INTERACTIONS

7.1 Cytochrome P450 1A2 Inhibitors and Inducers

In vitro metabolism studies showed that cytrochrome P450 1A2 (CYP1A2) is the major enzyme responsible for the metabolism of ropinirole. There is thus the potential for inducers or inhibitors of this enzyme to alter the clearance of ropinirole. Therefore, if therapy with a drug known to be a potent inducer or inhibitor of CYP1A2 is stopped or started during treatment with ropinirole extended-release tablets, adjustment of the dose of ropinirole extended-release tablets may be required. Coadministration of ciprofloxacin, an inhibitor of CYP1A2, with immediate-release ropinirole increases the AUC and Cmax of ropinirole [see Clinical Pharmacology (12.3)]. Cigarette smoking is expected to increase the clearance of ropinirole since CYP1A2 is known to be induced by smoking [see Clinical Pharmacology (12.3)].

7.2 Estrogens

Population pharmacokinetic analysis revealed that higher doses of estrogens (usually associated with hormone replacement therapy) reduced the clearance of ropinirole. Starting or stopping hormone replacement therapy may require adjustment of dosage of ropinirole extended-release tablets [see Clinical Pharmacology (12.3)].

7.3 Dopamine Antagonists

Because ropinirole is a dopamine agonist, it is possible that dopamine antagonists such as neuroleptics (e.g., phenothiazines, butyrophenones, thioxanthenes) or metoclopramide may reduce the efficacy of ropinirole extended-release tablets.

8 USE IN SPECIFIC POPULATIONS

8.1 Pregnancy

Risk Summary
There are no adequate data on the developmental risk associated with the use of ropinirole extended-release tablets in pregnant women. In animal studies, ropinirole had adverse effects on development when administered to pregnant rats at doses similar to (neurobehavioral impairment) or greater than (teratogenicity and embryolethality at >36 times) the MRHD for Parkinson’s disease. Ropinirole doses associated with teratogenicity and embryolethality in pregnant rats were associated with maternal toxicity. In pregnant rabbits, ropinirole potentiated the teratogenic effects of L-dopa when these drugs were administered in combination [see Data].

In the U.S. general population, the estimated background risk of major birth defects and of miscarriage in clinically recognized pregnancies is 2% to 4% and 15% to 20%, respectively. The background risk of major birth defects and miscarriage in the indicated populations is unknown.

Data

Animal Data: Oral administration of ropinirole (0, 20, 60, 90, 120, or 150 mg/kg/day) to pregnant rats during organogenesis resulted in embryolethality, increased incidence of fetal malformations (digit, cardiovascular, and neural tube defects) and variations, and decreased fetal weight at the 2 highest doses. These doses were also associated with maternal toxicity. The highest no-effect dose for adverse effects on embryofetal development (90 mg/kg/day) is approximately 36 times the MRHD for Parkinson’s disease (24 mg/day) on a body surface area (mg/m^2) basis.

No effect on embryofetal development was observed in rabbits when ropinirole was administered alone during organogenesis at oral doses of 0, 1, 5, or 20 mg/kg/day (up to 16 times the MRHD on a mg/m^2 basis). In pregnant rabbits, there was a greater incidence and severity of fetal malformations (primarily digit defects) when ropinirole (10 mg/kg/day) was administered orally during gestation in combination with L-dopa (250 mg/kg/day) than when L-dopa was administered alone. This drug combination was also associated with maternal toxicity.

Oral administration of ropinirole (0, 0.1, 1, or 10 mg/kg/day) to rats during late gestation and continuing throughout lactation resulted in neurobehavioral impairment (decreased startle response) and decreased body weight in offspring at the highest dose. The no-effect dose of 1 mg/kg/day is less than the MRHD on a mg/m^2 basis.

8.2 Lactation

Risk Summary

There are no data on the presence of ropinirole in human milk, the effects of ropinirole on the breastfed infant, or the effects of ropinirole on milk production. However, inhibition of lactation is expected because ropinirole inhibits secretion of prolactin in humans. Ropinirole or metabolites, or both, are present in rat milk.

The developmental and health benefits of breastfeeding should be considered along with the mother’s clinical need for ropinirole extended-release tablets and any potential adverse effects on the breastfed infant from ropinirole or from the underlying maternal condition.

8.4 Pediatric Use

Safety and effectiveness in pediatric patients have not been established.

8.5 Geriatric Use

Dose adjustment is not necessary in elderly (65 years and older) patients, as the dose of ropinirole extended-release tablets is individually titrated to clinical therapeutic response and tolerability. Pharmacokinetic trials conducted in patients demonstrated that oral clearance of ropinirole is reduced by 15% in patients older than 65 years compared with younger patients [see Clinical Pharmacology (12.3)].

In flexible-dose clinical trials of ropinirole extended-release tablets, 387 patients were 65 years and older and 107 were 75 years and older. Among patients receiving ropinirole extended-release tablets, hallucination was more common in elderly patients (10%) compared with non-elderly patients (2%). In these trials, the incidence of overall adverse reactions increased with increasing age for both patients receiving ropinirole extended-release tablets and placebo.

In the fixed-dose clinical trials of ropinirole extended-release tablets, 176 patients were 65 years and older and 73 were 75 and older. Among patients with advanced Parkinson’s disease receiving ropinirole extended-release tablets, vomiting and nausea were more common in patients greater than 65 years (5% and 9%, respectively) compared with patients less than 65 (1% and 7%, respectively).

8.6 Renal Impairment

No dose adjustment is necessary in patients with moderate renal impairment (creatinine clearance of 30 to 50 mL/min). For patients with end-stage renal disease on hemodialysis, a reduced maximum dose is recommended [see Dosage and Administration (2.2), Clinical Pharmacology (12.3)].

The use of ropinirole extended-release tablets in patients with severe renal impairment (creatinine clearance <30 mL/min) without regular dialysis has not been studied.

8.7 Hepatic Impairment

The pharmacokinetics of ropinirole have not been studied in patients with hepatic impairment.

10 OVERDOSAGE

The symptoms of overdose with ropinirole extended-release tablets are generally related to its dopaminergic activity. General supportive measures are recommended. Vital signs should be maintained, if necessary.

In clinical trials, there have been patients who accidentally or intentionally took more than their prescribed dose of ropinirole. The largest overdose reported with immediate-release ropinirole in clinical trials was 435 mg taken over a 7-day period (62.1 mg/day). Of patients who received a dose greater than 24 mg/day, reported symptoms included adverse events commonly reported during dopaminergic therapy (nausea, dizziness), as well as visual hallucinations, hyperhidrosis, claustrophobia, chorea, palpitations, asthenia, and nightmares. Additional symptoms reported for overdoses included vomiting, increased coughing, fatigue, syncope, vasovagal syncope, dyskinesia, agitation, chest pain, orthostatic hypotension, somnolence, and confusional state.

11 DESCRIPTION

Ropinirole extended-release tablets, USP, contains ropinirole, a non-ergoline dopamine agonist as the hydrochloride salt. The chemical name of ropinirole hydrochloride is 4-[2-(dipropylamino)ethyl]-1,3-dihydro-2H-indol-2-one and the molecular formula is C16H24N2O•HCl. The molecular weight is 296.84 (260.38 as the free base).

The structural formula is:

Ropinirole hydrochloride USP is a pale cream to light pinkish – yellow powder with a melting range of 243° to 250°C and a solubility of 133 mg/mL in water.

Ropinirole extended-release tablets, USP, are formulated as a monolithic slow release matrix tablet with coating. Each biconvex, capsule-shaped tablet contains 2.28, 4.56, 6.84, 9.12, or 13.68 mg of ropinirole hydrochloride USP equivalent to ropinirole 2, 4, 6, 8, or 12 mg, respectively. Inactive ingredients consist of hypromellose, croscarmellose sodium, maltodextrin, lactose monohydrate, hydrogenated castor oil, colloidal silicon dioxide, magnesium stearate, and polyethylene glycol. Additionally, Lake Pigment HT 5516 FD&C Blue 1/Brill (sodium carbonate, sodium bicarbonate, FD&C Blue #1 and simethicone for 2 mg tablet), Lake Pigment HT 5284 Yellow 6 (sodium carbonate, sodium bicarbonate and FD&C Yellow #6 for 12 mg tablet), and ferric oxide red, ferric oxide yellow and ferrosoferric oxide (for 4 mg and 8 mg tablet).
Meets USP Dissolution Test 4.

12 CLINICAL PHARMACOLOGY

12.1 Mechanism of Action

Ropinirole is a non-ergoline dopamine agonist. The precise mechanism of action of ropinirole as a treatment for Parkinson’s disease is unknown, although it is thought to be related to its ability to stimulate dopamine D2 receptors within the caudate-putamen in the brain.

12.2 Pharmacodynamics

Clinical experience with dopamine agonists, including ropinirole, suggests an association with impaired ability to regulate blood pressure resulting in orthostatic hypotension, especially during dose escalation. In some subjects in clinical trials, blood pressure changes were associated with the emergence of orthostatic symptoms, bradycardia, and, in one case in a healthy volunteer, transient sinus arrest with syncope [see Warnings and Precautions (5.2, 5.3)].

The mechanism of orthostatic hypotension induced by ropinirole is presumed to be due to a D2-mediated blunting of the noradrenergic response to standing and subsequent decrease in peripheral vascular resistance. Nausea is a common concomitant symptom of orthostatic signs and symptoms.

At oral doses as low as 0.2 mg, ropinirole suppressed serum prolactin concentrations in healthy male volunteers.

Immediate-release ropinirole had no dose-related effect on electrocardiogram wave form and rhythm in young, healthy, male volunteers in the range of 0.01 to 2.5 mg.

Immediate-release ropinirole had no dose-or exposure-related effect on mean QT intervals in healthy male and female volunteers titrated to doses up to 4 mg/day. The effect of ropinirole on QTc intervals at higher exposures achieved either due to drug interactions, hepatic impairment, or at higher doses has not been systematically evaluated.

12.3 Pharmacokinetics

Increase in systemic exposure of ropinirole following oral administration of 2 to 12 mg of ropinirole extended-release tablets was approximately dose-proportional. For ropinirole extended-release tablets, steady-state concentrations of ropinirole are expected to be achieved within 4 days of dosing.

Absorption

In clinical trials with immediate-release ropinirole, more than 88% of a radiolabeled dose was recovered in urine, and the absolute bioavailability was 45% to 55%, indicating approximately 50% first-pass effect.

The bioavailability of ropinirole extended-release tablets is similar to that of immediate-release ropinirole tablets. In a repeat-dose trial in subjects with Parkinson’s disease using ropinirole extended-release tablets 8 mg, the dose-normalized AUC(0-24) and Cmin for ropinirole extended-release tablets and immediate-release ropinirole were similar. Dose-normalized Cmax was, on average, 12% lower for ropinirole extended-release tablets than for the immediate-release formulation and the median time-to-peak concentration was 6 to 10 hours. In a single-dose trial, administration of ropinirole extended-release tablets to healthy volunteers with food (i.e., high-fat meal) increased AUC by approximately 30% and Cmax by approximately 44%, compared with dosing under fasted conditions. In a repeat-dose trial in patients with Parkinson’s disease, food (i.e., high-fat meal) increased AUC by approximately 20% and Cmax by approximately 44%; Tmax was prolonged by 3 hours (median prolongation) compared with dosing under fasted conditions [see Dosage and Administration (2)].

Distribution

Ropinirole is widely distributed throughout the body, with an apparent volume of distribution of 7.5 L/kg. It is up to 40% bound to plasma proteins and has a blood-to-plasma ratio of 1:1.

Metabolism

Ropinirole is extensively metabolized by the liver. The major metabolic pathways are N-despropylation and hydroxylation to form the inactive N-despropyl metabolite and hydroxy metabolites. The N-despropyl metabolite is converted to carbamyl glucuronide, carboxylic acid, and N-despropyl hydroxy metabolites. The hydroxy metabolite of ropinirole is rapidly glucuronidated.

In vitro studies indicate that the major cytochrome P450 enzyme involved in the metabolism of ropinirole is CYP1A2, an enzyme known to be induced by smoking and omeprazole, and inhibited by, for example, fluvoxamine, mexiletine, and the older fluoroquinolones such as ciprofloxacin and norfloxacin.

Elimination

The clearance of ropinirole after oral administration is 47 L/h and its elimination half-life is approximately 6 hours. Less than 10% of the administered dose is excreted as unchanged drug in urine. N-despropyl ropinirole is the predominant metabolite found in urine (40%), followed by the carboxylic acid metabolite (10%), and the glucuronide of the hydroxy metabolite (10%).

Specific Populations

Because therapy with ropinirole extended-release tablets is initiated at a low dose and gradually titrated upward according to clinical tolerability to obtain the optimum therapeutic effect, adjustment of the initial dose based on gender, weight, or age is not necessary.

Geriatric Patients: Oral clearance of ropinirole is reduced by 15% in patients older than 65 years compared with younger patients. Dosage adjustment is not necessary in the elderly (older than 65 years), as the dose of ropinirole is to be individually titrated to clinical response.

Male and Female Patients: Male and female patients showed similar clearance.

Racial or Ethnic Groups: The influence of race on the pharmacokinetics of ropinirole has not been evaluated.

Cigarette Smoking: Smoking is expected to increase the clearance of ropinirole since CYP1A2 is known to be induced by smoking. In a trial in patients with Restless Legs Syndrome, smokers (n =7) had an approximately 30% lower Cmax and a 38% lower AUC than did nonsmokers (n = 11) when those parameters were normalized for dose.

Patients with Renal Impairment: Based on population pharmacokinetic analysis, no difference was observed in the pharmacokinetics of ropinirole in subjects with moderate renal impairment (creatinine clearance between 30 to 50 mL/min) compared with an age-matched population with creatinine clearance above 50 mL/min. Therefore, no dosage adjustment is necessary in patients with moderate renal impairment.

A trial of immediate-release ropinirole in subjects with end-stage renal disease on hemodialysis has shown that clearance of ropinirole was reduced by approximately 30%. The recommended maximum dose is lower in these patients [see Dosage and Administration (2.2)].

The use of ropinirole in subjects with severe renal impairment (creatinine clearance <30 mL/min) without regular dialysis has not been studied.

Patients with Hepatic Impairment: The pharmacokinetics of ropinirole have not been studied in patients with hepatic impairment. Because ropinirole is extensively metabolized by the liver, these patients may have higher plasma levels and lower clearance of ropinirole than patients with normal hepatic function.

Other Diseases: Population pharmacokinetic analysis revealed no change in the clearance of ropinirole in patients with concomitant diseases such as hypertension, depression, osteoporosis/arthritis, and insomnia compared with patients with Parkinson’s disease only.

Drug Interaction Studies

Digoxin: Coadministration of immediate-release ropinirole (2 mg 3 times daily) with digoxin (0.125 to 0.25 mg once daily) did not alter the steady-state pharmacokinetics of digoxin in 10 patients.

Theophylline: Administration of theophylline (300 mg twice daily), a substrate of CYP1A2 did not alter the steady-state pharmacokinetics of immediate-release ropinirole (2 mg 3 times daily) in 12 patients with Parkinson’s disease. Immediate-release ropinirole (2 mg 3 times daily) did not alter the pharmacokinetics of theophylline (5 mg/kg intravenously) in 12 patients with Parkinson’s disease.

Ciprofloxacin: Coadministration of ciprofloxacin (500 mg twice daily), an inhibitor of CYP1A2, with immediaterelease ropinirole (2 mg 3 times daily) increased ropinirole AUC by 84% on average and Cmax by 60% (n = 12 patients).

Estrogens: Population pharmacokinetic analysis revealed that estrogens (mainly ethinylestradiol: intake 0.6 to 3 mg over 4-month to 23-year period) reduced the oral clearance of ropinirole by 36% in 16 patients.

L-dopa: Coadministration of carbidopa + L-dopa (10/100 mg twice daily) with immediate-release ropinirole (2 mg 3 times daily) had no effect on the steady-state pharmacokinetics of ropinirole (n = 28 patients). Oral administration of immediate-release ropinirole 2 mg 3 times daily increased mean steady-state Cmax of L-dopa by 20%, but its AUC was unaffected (n = 23 patients).

Commonly Administered Drugs: Population analysis showed that commonly administered drugs (e.g., selegiline, amantadine, tricyclic antidepressants, benzodiazepines, ibuprofen, thiazides, antihistamines, anticholinergics) did not affect the clearance of ropinirole. An in vitro study indicates that ropinirole is not a substrate for P-glycoprotein.
Ropinirole and its circulating metabolites do not inhibit or induce P450 enzymes; therefore, ropinirole is unlikely to affect the pharmacokinetics of other drugs by a P450 mechanism.

13 NONCLINICAL TOXICOLOGY

13.1 Carcinogenesis, Mutagenesis, Impairment of Fertility

Carcinogenesis

Two-year carcinogenicity studies of ropinirole were conducted in mice at oral doses of 0, 5, 15, and 50 mg/kg/day and in rats at oral doses of 0, 1.5, 15, and 50 mg/kg/day.

In rats, there was an increase in testicular Leydig cell adenomas at all doses tested. The lowest dose tested (1.5 mg/kg/day) is less than the MRHD (24 mg/day) on a mg/m^2 basis. The endocrine mechanisms believed to be involved in the production of these tumors in rats are not considered relevant to humans.

In mice, there was an increase in benign uterine endometrial polyps at a dose of 50 mg/kg/day. The highest dose not associated with this finding (15 mg/kg/day) is 3 times the MRHD on a mg/m^2 basis.

Mutagenesis

Ropinirole was not mutagenic or clastogenic in in vitro (Ames, chromosomal aberration in human lymphocytes, mouse lymphoma tk) assays, or in the in vivo mouse micronucleus test.

Impairment of Fertility

When administered to female rats prior to and during mating and throughout pregnancy, ropinirole caused disruption of implantation at oral doses of 20 mg/kg/day (8 times the MRHD on a mg/m^2 basis) or greater. This effect in rats is thought to be due to the prolactin-lowering effect of ropinirole. In rat studies using a low oral dose (5 mg/kg) during the prolactin-dependent phase of early pregnancy (gestation days 0 to 8), ropinirole did not affect female fertility at oral doses up to 100 mg/kg/day (40 times the MRHD on a mg/m^2 basis). No effect on male fertility was observed in rats at oral doses up to 125 mg/kg/day (50 times the MRHD on a mg/m^2 basis).

14 CLINICAL STUDIES

The effectiveness of ropinirole was initially established with the immediate-release formulation (REQUIP tablets) for the treatment of early and advanced Parkinson’s disease in 3 randomized, double-blind, placebo-controlled trials.

The effectiveness of ropinirole extended-release tablets in the treatment of Parkinson’s disease was supported by 2 randomized, double-blind, multicenter flexible-dose clinical trials and clinical pharmacokinetic considerations. One trial conducted in patients with advanced Parkinson’s disease compared ropinirole extended-release tablets with placebo as adjunctive therapy to L-dopa (Study 1). A second trial compared ropinirole extended-release tablets with REQUIP tablets in patients with early Parkinson’s disease not receiving L-dopa (Study 3). Ropinirole extended-release tablets has also been evaluation in 2 postmarketing, randomized, double-blind, multicenter, fixed-dose, dose-response clinical trials conducted in advanced and early Parkinson’s disease patients (Study 2 and Study 4, respectively).

In these trials, a variety of measures were used to assess the effects of treatment (e.g., Unified Parkinson’s Disease Rating Scale [UPDRS] scores, patient diaries recording time "on" and "off", tolerability of L-dopa dose reductions). The UPDRS is a multi-item rating scale intended to evaluate mentation (Part I), activities of daily living (Part II), motor performance (Part III), and complications of therapy (Part IV). Part III of the UPDRS contains 14 items designed to assess the severity of the cardinal motor findings in patients with Parkinson’s disease (e.g., tremor, rigidity, bradykinesia, postural instability) scored for different body regions and has a maximum (worst) score of 108.

14.1 Trials in Patients with Advanced Parkinson's Disease (with L-dopa)

Study 1 (Flexible-Dose Trial)
The effectiveness of ropinirole extended-release tablets as adjunctive therapy to L-dopa in patients with Parkinson’s disease was established in a 24-week, randomized, double-blind, placebo-controlled, parallel-group, flexible-dose, clinical trial in 393 patients (Hoehn & Yahr criteria Stages II-IV) who were not adequately controlled by L-dopa therapy. Patients were allowed to be on concomitant selegiline, amantadine, anticholinergics, and catechol-O-methyltransferase inhibitors provided the doses were stable for at least 4 weeks prior to screening and throughout the trial. The primary efficacy endpoint evaluated was the mean change from baseline in total awake time spent “off”.

Patients in this trial had a mean disease duration of 8.6 years, had a mean duration of exposure to L-dopa of 6.5 years, had experienced a minimum of 3 hours awake time “off” with a baseline average of approximately 7 hours awake time “off”, and had a mean baseline UPDRS motor score of approximately 30 points. The mean baseline dose of L-dopa was 824 mg/day in the group receiving ropinirole extended-release tablets was 824 mg/day and 776 mg/day in the placebo group. Patients initiated treatment at 2 mg/day for 1 week, followed by increases of 2 mg/day at weekly intervals, to a minimum dose of 6 mg/day. The following week, the total daily dose of ropinirole extended-release tablets could be further increased (based upon therapeutic response and tolerability) to 8 mg/day. Once a daily dose of 8 mg/day was reached, the background L-dopa dosage was reduced. Thereafter, the daily dose could be increased by up to 4 mg/day approximately every 2 weeks until an optimal dose was achieved (based upon therapeutic response and tolerability). The mean dose of ropinirole extended-release tablets at the end of Week 24 was 18.8 mg/day. Dose titrations were based upon the degree of symptom control, planned L-dopa dosage reduction, and/or tolerability. The maximum allowed daily dosage for ropinirole extended-release tablets was 24 mg/day.

The primary efficacy endpoint was mean change from baseline in total awake time spent “off” at Week 24. At baseline, the mean total awake time spent “off” was approximately 7 hours in each treatment group. At Week 24, the total awake time spent “off”, on average, had decreased by approximately 2 hours in the group receiving ropinirole extended-release tablets and by approximately one-half hour in the placebo group. The adjusted mean difference in total awake time spent “off” between ropinirole extended-release tablets and placebo was -1.7 hours, which was statistically significant (analysis of covariance [ANCOVA], P<0.0001). Results for this endpoint, showing the statistical superiority of ropinirole extended-release tablets over placebo, are presented in Table 5.

Table 5. Change from Baseline in Total Awake Time Spent "Off" (Primary Efficacy Endpoint) at Week 24 (Study 1)

 | Ropinirole Extended-Release Tablets (n = 201) | Placebo (n = 190)
Mean “off” time at baseline (h) | 7.0 | 7.0
Mean change from baseline in “off” time (h) | -2.1 | -0.4
Treatment difference (Ropinirole Extended-Release Tablets - PLACEBO) |  | - 1.7

The difference between groups in favor of ropinirole extended-release tablets, with regard to a decrease in total “off” hours, was primarily related to an increase in total “on” hours without troublesome dyskinesia. Patients treated with ropinirole extended-release tablets had a mean reduction in L-dopa dose of 278 mg/day (34%), while patients treated with placebo had a mean reduction of 164 mg/day (21%). In patients who reduced their L-dopa dose, reduction was sustained in 93% of patients treated with ropinirole extended-release tablets and in 72% of patients treated with placebo (P<0.001).

Study 2 (Fixed-Dose,Dose-Response Trial)

A double-blind, placebo-controlled, fixed-dose, parallel-group trial evaluated the dose response of ropinirole extended-release tablets as adjunctive therapy to L-dopa in 352 randomized patients with advanced Parkinson’s disease (Hoehn & Yahr criteria Stages II-IV) over a total dosing period of 18 weeks. Patients initiated treatment with placebo or ropinirole extended-release tablets at 2 mg/day for 1 week, and increased to a target dose of 4, 8, 12, 16, or 24 mg/day over a 13-week up titration period. The dose remained stable over an additional 4-week maintenance period, followed by a 1-week down-titration period. The L-dopa dose was kept constant during the study, if possible. The primary efficacy endpoint was the mean change from baseline in total awake time spent“off” at Week 4 of the maintenance period with daily doses of 4, 8, 12, 16, and 24 mg compared with placebo. The primary statistical analysis of the primary efficacy endpoint was Mixed Model Repeated Measures (MMRM).

At baseline, the mean “off” time ranged from 5.6 to 6.5 hours across groups on ropinirole extended-release tablets and placebo. Table 6 shows the results for the primary efficacy endpoint. The greatest treatment difference (Ropinirole extended-release tablets – PLACEBO) for the primary efficacy endpoint was observed with the 8 mg dose; however, higher doses were not shown to provide additional benefit.

Table 6. Change from Baseline in Total Awake Time Spent “Off” (Primary Efficacy Endpoint) at the End of the Maintenance Period (Study 2)

 |  | Daily Ropinirole Extended-Release Tablets Dose
Endpoint | Placebo N = 65 | 4 mg N = 21 | 8 mg N = 60 | 12 mg N = 61 | 16 mg N = 65 | 24 mg N = 25
Least squares mean change from baseline for “off” time | -1.91 | -2.04 | -2.92 | -2.34 | -2.80 | -2.37
Treatment difference (Ropinirole extended-release tablets – PLACEBO) |  | -0.13 | -1.01 | -0.43 | -0.89 | -0.46
P valuea |  | 0.81 | 0.01 | 0.29 | 0.03 | 0.39

a P value not adjusted for multiple comparisons. A hierarchical step-down approach for statistical testing was used starting with 16-mg dose.

14.2 Trials in Patients with Early Parkinson's Disease (without L-dopa)

Study 3 (Flexible-Dose Trial)

A 36-week multicenter, double-blind, titration/3-period maintenance, flexible-dose, cross-over trial compared the efficacy of ropinirole extended-release tablets with the immediate-release formulation of REQUIP in 161 patients with early phase Parkinson’s disease (Hoehn & Yahr Stages I-III) with limited prior exposure to L-dopa or dopamine agonists. Eligible patients were randomized (1:1:1:1) to 4 treatment sequences (2 were titrated on immediate-release formulation of REQUIP and 2 on ropinirole extended-release tablets). Titration rate of immediate-release formulation of REQUIP was slower than that of the ropinirole extended-release tablets. Patients were titrated, during the 12-week titration period, to their optimal dosage, based upon tolerance and therapeutic response. This was followed by 3 consecutive 8-week maintenance periods, during which patients were either maintained on the prior formulation or switched to the alternative formulation. All switches were performed overnight by using the approximately equivalent doses of ropinirole. The primary efficacy endpoint was the change of UPDRS motor score within each maintenance period.

Patients in all 4 groups started out with similar UPDRS motor scores (about 21) at baseline. All groups exhibited similar improvement in UPDRS total motor scores from baseline until the completion of the titration phase, with a change in score of about -9 observed for the groups started on immediate-release formulation of REQUIP and of about -10 for the groups started on ropinirole extended-release tablets. No difference was observed between groups when switches were made between identical formulations or between different formulations. This suggests therapeutic dosage equivalence between the immediate-release formulation of REQUIP and ropinirole extended-release tablets.

The optimal daily dose at the end of the titration period for patients on immediate-release formulation of REQUIP was substantially lower (mean: 7 mg) compared with the dose at the end of the titration period for patients on ropinirole extended-release tablets (mean: 18 mg). In this trial, the marked difference in the final optimal dosages suggests that the higher doses afforded no additional benefit when compared with the lower doses [see Dosage and Administration (2.2)].

Study 4 (Fixed-Dose, Dose-Response Trial)

A double-blind, placebo-controlled, fixed-dose, parallel-group trial evaluated the dose response of ropinirole extended-release tablets without L-dopa in 186 randomized patients with early Parkinson’s disease (Hoehn & Yahr Stages I-III) over a total dosing period of 18 weeks. Patients initiated treatment with placebo or ropinirole extended-release tablets at 2 mg/day for 1 week and were either maintained at a target dose of 2mg/day or further increased to a target dose of 4, 8, 12, or 24 mg/day over a 13-week up-titration period. The dose remained stable over an additional 4 week maintenance period, followed by a 1-week down-titration period. The primary statistical analysis of the primary efficacy endpoint was Mixed Model Repeated Measures (MMRM).

The primary efficacy endpoint was the change from baseline in UPDRS motor score at Week 4 of the maintenance period with daily doses of 2, 4, 8, 12, and 24 mg compared with placebo. At baseline, the mean UPDRS motor score ranged from approximately 21 to 25 across all groups receiving ropinirole extended-release tablets and placebo. Table 7 shows results for the primary efficacy endpoint. The greatest treatment difference (Ropinirole extended-release tablets – PLACEBO) for the primary efficacy endpoint occurred with the 12-mg dose. At Week 4 of the maintenance period, the primary efficacy analysis (MMRM) did not show a significant difference between placebo (mean adjusted change: -3.98) and any dose of ropinirole extended-release tablets (mean adjusted changes ranged from -4.09 to -6.14). Data were also analyzed by nonparametric ANCOVA as pre-specified because of non- normality. This analysis and showed that there was a significant reduction from baseline in the UPDRS motor score for the group receiving ropinirole extended-release tablets 12 mg/day (P = 0.047); however, higher doses were not shown to provide additional benefit.

Table 7. Change from Baseline in Unified Parkinson’s Disease Rating Scale (UPDRS) Part III Motor Score (Primary Efficacy Endpoint) at the End of the Maintenance Period (Study 4)

Endpoint | Placebo N = 35 | Daily Ropinirole Extended-Release Tablets Dose
Endpoint | Placebo N = 35 | 2 mg N = 13 | 4 mg N = 35 | 8 mg N = 33 | 12 mg N = 34 | 24 mg N = 10
Least squares mean change from baseline in UPDRS Part III motor score | -3.98 | -4.09 | -4.97 | -5.90 | -6.14 | -4.85
Treatment difference (Ropinirole Extended-Release Tablets – PLACEBO) |  | -0.11 | -0.99 | -1.92 | -2.16 | -0.87
P valuea |  | 0.95 | 0.48 | 0.18 | 0.13 | 0.68

a P value not adjusted for multiple comparisons. A hierarchical step-down approach for statistical testing was used starting with 12-mg dose.

16 HOW SUPPLIED/STORAGE AND HANDLING

Each biconvex, capsule-shaped, film-coated tablet contains ropinirole hydrochloride, USP, equivalent to the labeled amount of ropinirole as follows:

2 mg: blue tablet, biconvex capsule-shaped with ‘ELR2’ on one side and plain on the other and are supplied in bottles of 30 (NDC 64850-250-30).

4 mg: beige tablet biconvex, capsule-shaped, with ‘ELR4’ on one side and plain on the other and are supplied in bottles of 30 (NDC 64850-251-30).

6 mg: white tablet, biconvex, capsule-shaped with ‘ELR6’ on one side and plain on the other and are supplied in bottles of 30 (NDC 64850-252-30).

8 mg: pink tablet, biconvex, capsule-shaped with ‘ELR8’ on one side and plain on the other and are supplied in bottles of 30 (NDC 64850-253-30).

12 mg: peach tablet, biconvex, capsule-shaped with ‘ELR12’ on one side and plain on the other and are supplied in bottles of 30 (NDC 64850-254-30).

Storage

Store at 20° to 25°C (68° to 77°F); excursions permitted to 15° to 30°C (59° to 86° F) [see USP Controlled Room Temperature].

Dispense in a tight, light-resistant container as defined in the USP.

17 PATIENT COUNSELING INFORMATION

Advise the patient to read the FDA-approved patient labeling (Patient Information).

Dosing Instructions

Instruct patients to take ropinirole extended-release tablets only as prescribed. If a dose is missed, advise patients not to double their next dose. Ropinirole extended-release tablets can be taken with or without food. Inform patients to swallow ropinirole extended-release tablets whole and not to chew, crush, or divide the tablets [see Dosage and Administration (2.1)].

Ropinirole is the active ingredient in both ropinirole extended-release tablets and REQUIP tablets (the immediate-release formulation). Ask your patients if they are taking another medication containing ropinirole.

Hypersensitivity/Allergic Reactions

Advise patients about the potential for developing a hypersensitivity/allergic reaction including manifestations such as urticaria, angioedema, rash, and pruritus when taking any ropinirole product. Inform patients who experience these or similar reactions after starting REQUIP or ropinirole extended-release tablets, to immediately contact their healthcare professional [see Contraindications (4)].

Falling Asleep during Activities of Daily Living and Somnolence

Alert patients to the potential sedating effects caused by ropinirole extended-release tablets, including somnolence and the possibility of falling asleep while engaged in activities of daily living. Because somnolence is a frequent adverse reaction with potentially serious consequences, patients should not drive a car, operate machinery, or engage in other potentially dangerous activities until they have gained sufficient experience with ropinirole extended-release tablets to gauge whether or not it adversely affects their mental and/or motor performance. Advise patients that if increased somnolence or episodes of falling asleep during activities of daily living (e.g., conversations, eating, driving a motor vehicle) are experienced at any time during treatment, they should not drive or participate in potentially dangerous activities until they have contacted their physician.

Advise patients of possible additive effects when patients are taking other sedating medications, alcohol, or other central nervous system depressants (e.g., benzodiazepines, antipsychotics, antidepressants) in combination with ropinirole extended-release tablets or when taking a concomitant medication (e.g., ciprofloxacin) that increases plasma levels of ropinirole [see Warnings and Precautions (5.1)].

Syncope and Hypotension/Orthostatic Hypotension

Advise patients that they may experience syncope and may develop hypotension with or without symptoms such as dizziness, nausea, syncope, and sometimes sweating while taking ropinirole extended-release tablets, especially if they are elderly. Hypotension and/or orthostatic symptoms may occur more frequently during initial therapy or with an increase in dose at any time (cases have been seen after weeks of treatment). Postural/orthostatic symptoms may be related to sitting up or standing. Accordingly, caution patients against standing rapidly after sitting or lying down, especially if they have been doing so for prolonged periods and especially at the initiation of treatment with ropinirole extended-release tablets [see Warnings and Precautions (5.2, 5.3)].

Elevation of Blood Pressure and Changes in Heart Rate

Alert patients to the possibility of increases in blood pressure during treatment with ropinirole extended-release tablets. Exacerbation of hypertension may occur. Medication dose adjustment may be necessary if elevation of blood pressure is sustained over multiple evaluations. Alert patients with cardiovascular disease, who may not tolerate marked changes in heart rate to the possibility that they may experience significant increases or decreases in heart rate during treatment with ropinirole extended-release tablets [see Warnings and Precautions (5.4)].

Hallucinations/Psychotic-Like Behavior

Inform patients that they may experience hallucinations (unreal visions, sounds, or sensations) and that other psychotic-like behavior can occur while taking ropinirole extended-release tablets. In patients with Parkinson's disease, the elderly are at greater risk than younger patients. This risk is greater in patients who are taking ropinirole extended-release tablets with L-dopa or taking higher doses of ropinirole extended-release tablets, and may also be further increased in patients taking any other drugs that increase dopaminergic tone. Tell patients to report hallucinations or psychotic-like behavior to their healthcare provider promptly should they develop [see Warnings and Precautions (5.5)].

Dyskinesia

Inform patients that ropinirole extended-release tablets may cause and/or exacerbate pre-existing dyskinesias [see Warnings and Precautions (5.6)].

Impulse Control/Compulsive Behaviors

Advise patients that they may experience impulse control and/or compulsive behaviors while taking ropinirole extended-release tablets. Advise patients to inform their physician or healthcare provider if they develop new or increased gambling urges, sexual urges, uncontrolled spending, binge or compulsive eating, or other urges while being treated with ropinirole extended-release tablets. Physicians should consider dose reduction or stopping the medication if a patient develops such urges while taking ropinirole extended-release tablets [see Warnings and Precautions (5.7)].

Withdrawal-Emergent Hyperpyrexia and Confusion

Advise patients to contact their healthcare provider if they wish to discontinue ropinirole extended-release tablets or decrease the dose of ropinirole extended-release tablets. Advise patients who have been prescribed a lower dose or who have been withdrawn from the drug to notify their healthcare provider if they present with fever, muscular rigidity, or altered consciousness [see Warnings and Precautions (5.8)].

Withdrawal Symptoms

Advise patients that withdrawal symptoms may occur during or after discontinuation or dose reduction of ropinirole extended-release tablets. Advise patients who have been prescribed a lower dose or who have been withdrawn from the drug to notify their healthcare provider if they have withdrawal symptoms such as apathy, anxiety, depression, fatigue, insomnia, sweating, or pain. Notify patients that in case of severe withdrawal symptoms, a trial re-administration of a dopamine agonist at the lowest effective dose may be considered [see Warnings and Precautions (5.9)].

Nursing Mothers

Because of the possibility that ropinirole may be excreted in breast milk, discuss the developmental and health benefits of breastfeeding along with the mother’s clinical need for ropinirole extended-release tablets and any potential adverse effects on the breastfed child from ropinirole or from the underlying maternal condition [see Use in Specific Populations (8.2)]. Advise patients that ropinirole extended-release tablets could inhibit lactation because ropinirole inhibits prolactin secretion.

Pregnancy

Because experience with ropinirole in pregnant women is limited and ropinirole has been shown to have adverse effects on embryofetal development in animals, including teratogenic effects, advise patients of this potential risk. Advise patients to notify their physician if they become pregnant or intend to become pregnant during therapy [see Use in Specific Populations (8.1)].

Rx Only

Manufactured by:
Elite Laboratories, Inc.
Northvale, NJ 07647
IN0549
Revised: 11/2025

All Product/Brand names are the trademarks of their respective owners.

Patient Information

Ropinirole (roe pin' i role") Extended-Release Tablets

Important Note: Ropinirole extended-release tablets have not been studied in RLS and is not approved for the treatment of RLS.
However, an immediate-release form of ropinirole (REQUIP) is approved for the treatment of moderate to severe primary RLS.

What is the most important information I should know about ropinirole extended-release tablets?

Ropinirole extended-release tablets can cause serious side effects including:

- Falling asleep during normal activities. You may fall asleep while doing normal activities such as driving a car, doing physical tasks, or using hazardous machinery while taking ropinirole extended-release tablets. You may suddenly fall asleep without being drowsy or without warning. This may result in having accidents. Your chances of falling asleep while doing normal activities while taking ropinirole extended-release tablets are greater if you take other medicines that cause drowsiness. Tell your healthcare provider right away if this happens. Before starting ropinirole extended-release tablets, be sure to tell your healthcare provider if you take any medicines that make you drowsy.
- Fainting. Fainting can happen, and sometimes your heart rate may be decreased. This can happen especially when you start taking ropinirole extended-release tablets or your dose is increased. Tell your healthcare provider if you faint, feel dizzy or feel light-headed.
- Decrease in blood pressure. Ropinirole extended-release tablets can decrease your blood pressure (hypotension), can happen, especially when you start taking ropinirole extended-release tablets or when your dose is changed. If you faint or feel dizzy, nauseated, or sweaty when you stand up from sitting or lying down (orthostatic hypotension), this may mean that your blood pressure is decreased. When you change position from lying down or sitting to standing up, you should do it carefully and slowly. Call your healthcare provider if you have any of the symptoms of decreased blood pressure listed above.
- Increase in blood pressure. Ropinirole extended-release tablets may increase your blood pressure.
- Changes in heart rate (decrease or increase). Ropinirole extended-release tablets can decrease or increase your heart rate.
- Hallucinations and other psychotic-like behavior. Ropinirole extended-release tablets can cause or worsen psychotic-like behavior including hallucinations (seeing or hearing things that are not real), confusion, excessive suspicion, aggressive behavior, agitation, delusional beliefs (believing things that are not real), and disorganized thinking. The chances of having hallucinations or these other psychotic-like changes are higher in people with Parkinson’s disease who are taking ropinirole extended-release tablets or taking higher doses of these drugs. If you have hallucinations or any of these other psychotic-like changes, talk with your healthcare provider.
- Uncontrolled sudden movements. Ropinirole extended-release tablets may cause uncontrolled sudden movements or make such movements you already have worse or more frequent. Tell your healthcare provider if this happens. The doses of your anti-Parkinson’s medicine may need to be changed.
- Unusual urges. Some patients taking ropinirole extended-release tablets get urges to behave in a way unusual for them. Examples of this are an unusual urge to gamble, increased sexual urges and behaviors, or an uncontrollable urge to shop, spend money, or eat. If you notice or your family notices that you are developing any unusual behaviors, talk to your healthcare provider.
- Withdrawal Symptoms. Ropinirole extended-release tablets are dopamine agonist medicines. Dopamine agonist medicines, including ropinirole extended-release tablets, can cause withdrawal symptoms as your dose is slowly lowered (tapered) or when treatment with ropinirole extended-release tablets is stopped. Tell your doctor right away if you get any of the following withdrawal symptoms:
  - fever
  - confusion
  - severe muscle stiffness
  - insomnia
  - depression
  - anxiety
  - fatigue
  - sweating
  - pain
  - feeling like you do not care about things you usually care about (apathy)
  After you have stopped taking ropinirole extended-release tablets, your healthcare provider may need to restart you at a low dose of ropinirole extended-release tablets if you get severe withdrawal symptoms.

What are ropinirole extended-release tablets?

- Ropinirole extended-release tablets are long-acting prescription medicine containing ropinirole (taken 1 time a day) that is used only to treat Parkinson’s disease but not to treat RLS.

Having one of these conditions does not mean you have or will develop the other condition.

You should not be taking more than 1 medicine containing ropinirole. Tell your healthcare provider if you are taking any other medicine containing ropinirole.

It is not known if ropinirole extended-release tablets are safe and effective for use in children younger than 18 years of age.

Do not take ropinirole extended-release tablets if you:

• are allergic to ropinirole or any of the ingredients in ropinirole extended-release tablets. See the end of this page for a complete list of the ingredients in ropinirole extended-release tablets.

· Get help right away if any of the symptoms of an allergic reaction cause problems swallowing or breathing.

Call your healthcare provider if you have any of the symptoms of an allergic reaction. Symptoms of an allergic reaction may include:

• hives

• rash

• swelling of the face, lips, mouth, tongue, or throat

• itching

Before taking ropinirole extended-release tablets, tell your healthcare provider about all of your medical conditions, including if you.

- have daytime sleepiness from a sleep disorder to have unexpected or unpredictable sleepiness or periods of sleep.
- start or stop taking other medicines while you are taking ropinirole extended-release tablets. This may increase your chances of getting side effects.
- start or stop smoking while you are taking ropinirole extended-release tablets. Smoking may decrease the treatment effect of ropinirole extended-release tablets.
- feel dizzy, nauseated, sweaty, or faint when you stand up from sitting or lying down.
- drink alcoholic beverages. This may increase your chances of becoming drowsy or sleepy while taking ropinirole extended-release tablets.
- have high or low blood pressure.
- have or have had heart problems.
- are pregnant or plan to become pregnant. It is not known if ropinirole extended-release tablets can harm your unborn baby.
- are breastfeeding or plan to breastfeed. It is now known if ropinirole extended-release passes into your breast milk. The amount of breast milk you make may be decreased while taking ropinirole extended-release tablets. Talk to your healthcare provider to decide if you should breastfeed while taking ropinirole extended-release tablets.

Tell your healthcare provider about all the medicines you take, including prescription and over-the-counter medicines, vitamins, and herbal supplements. Some of these medicines may increase your chances of getting side effects while taking ropinirole extended-release tablets.

How should I take ropinirole extended-release tablets?

- Take ropinirole extended-release tablets exactly as directed by your healthcare provider.
- Take ropinirole extended-release tablets with or without food.
- Do not suddenly stop taking ropinirole extended-release tablets without talking to your healthcare provider. If you stop this medicine, you may develop withdrawal symptoms (See “What is the most important information I should know about ropinirole extended-release tablets?”).
- Before starting ropinirole extended-release tablets, you should talk to your healthcare provider about what to do if you miss a dose. If you have missed the previous dose and it is time for your next dose, do not double the dose.
- Your healthcare provider will start you on a low dose of ropinirole extended-release tablets. Your healthcare provider will change the dose until you are taking the right amount of medicine to control your symptoms. It may take several weeks before you reach a dose that controls your symptoms.
- Contact your healthcare provider if you stop taking ropinirole extended-release tablets for any reason. Do not restart without talking with your healthcare provider.
- Your healthcare provider may prescribe ropinirole extended-release tablets alone, or add ropinirole extended-release tablets to medicine that you are already taking for Parkinson's disease.
- You should not substitute REQUIP for ropinirole extended-release tablets or ropinirole extended-release tablets for REQUIP without talking with your healthcare provider.

If you are taking ropinirole extended-release tablets:

- Take ropinirole extended-release tablets 1 time each day for Parkinson’s disease, preferably at or around the same time of day.
- Swallow ropinirole extended-release tablets whole. Do not chew, crush, or split ropinirole extended-release tablets.
- Ropinirole extended-release tablets release drug over a 24-hour period. If you have a condition where medicine passes through your body too quickly, such as diarrhea, the tablet(s) may not dissolve completely and you may see tablet residue in your stool. If this happens, let your healthcare provider know as soon as possible.

What are the possible side effects of ropinirole extended-release tablets?

Ropinirole extended-release tablets can cause serious side effects including:

• See “What is the most important information I should know about ropinirole extended-release tablets?”

The most common side effects of ropinirole extended-release tablets include:

- fainting
- sleepiness or drowsiness
- hallucinations (seeing or hearing things that are not real)
- dizziness
- nausea or vomiting
- uncontrolled sudden movements
- upset stomach, abdominal pain or discomfort
- fatigue, tiredness, or weakness
- confusion
- headache
- leg swelling
- increased sweating
- constipation
- suddenly falling asleep
- high blood pressure (hypertension)

Tell your healthcare provider about any side effect that bothers you or that does not go away.

These are not all of the possible side effects with ropinirole extended-release tablets.

Call your doctor for medical advice about side effects. You may report side effects to FDA at 1-800-FDA-1088.

How should I store ropinirole extended-release tablets?

- Store at room temperature between 68° to 77°F (20° to 25°C)
- Keep ropinirole extended-release tablets in a tightly closed container and out of direct sunlight.

Keep ropinirole extended-release tablets and all medicines out of the reach of children.

General information about the safe and effective use of ropinirole extended-release tablets

Medicines are sometimes prescribed for purposes other than those listed in a Patient Information leaflet. Do not take ropinirole extended-release tablets for a condition for which it was not prescribed. Do not give ropinirole extended-release tablets to other people, even if they have the same symptoms that you have. It may harm them.

You can ask your pharmacist or healthcare provider for information about ropinirole extended-release tablets that is written for health professionals.

What are the ingredients in ropinirole extended-release tablets?

Active ingredient: ropinirole (as ropinirole hydrochloride USP)

Inactive ingredients: hypromellose, croscarmellose sodium, maltodextrin, lactose monohydrate, hydrogenated castor oil, colloidal silicon dioxide, magnesium stearate, and polyethylene glycol. Additionally, Lake Pigment HT 5516 FD&C Blue 1/Brill (sodium carbonate, sodium bicarbonate, FD&C Blue #1 and simethicone for 2 mg tablet), Lake Pigment HT 5284 Yellow 6 (sodium carbonate, sodium bicarbonate and FD&C Yellow #6 for 12 mg tablet), and ferric oxide red, ferric oxide yellow and ferrosoferric oxide (for 4 mg and 8 mg tablet).

Rx Only

Manufactured by:
Elite Laboratories, Inc.
Northvale, NJ 07647

For more information, call 1-888-852-6657.

This Patient Information has been approved by the U.S. Food and Drug Administration.

Revised: 11/25
All Product/Brand names are the trademarks of their respective owners.

PACKAGE LABEL.PRINCIPAL DISPLAY PANEL SECTION

Unvarnished Area Consists of: 2D Barcode, Lot Number, Expiry Date and Serial Number

2 mg container label

4 mg container label

6 mg container label

8 mg container label

12 mg container label